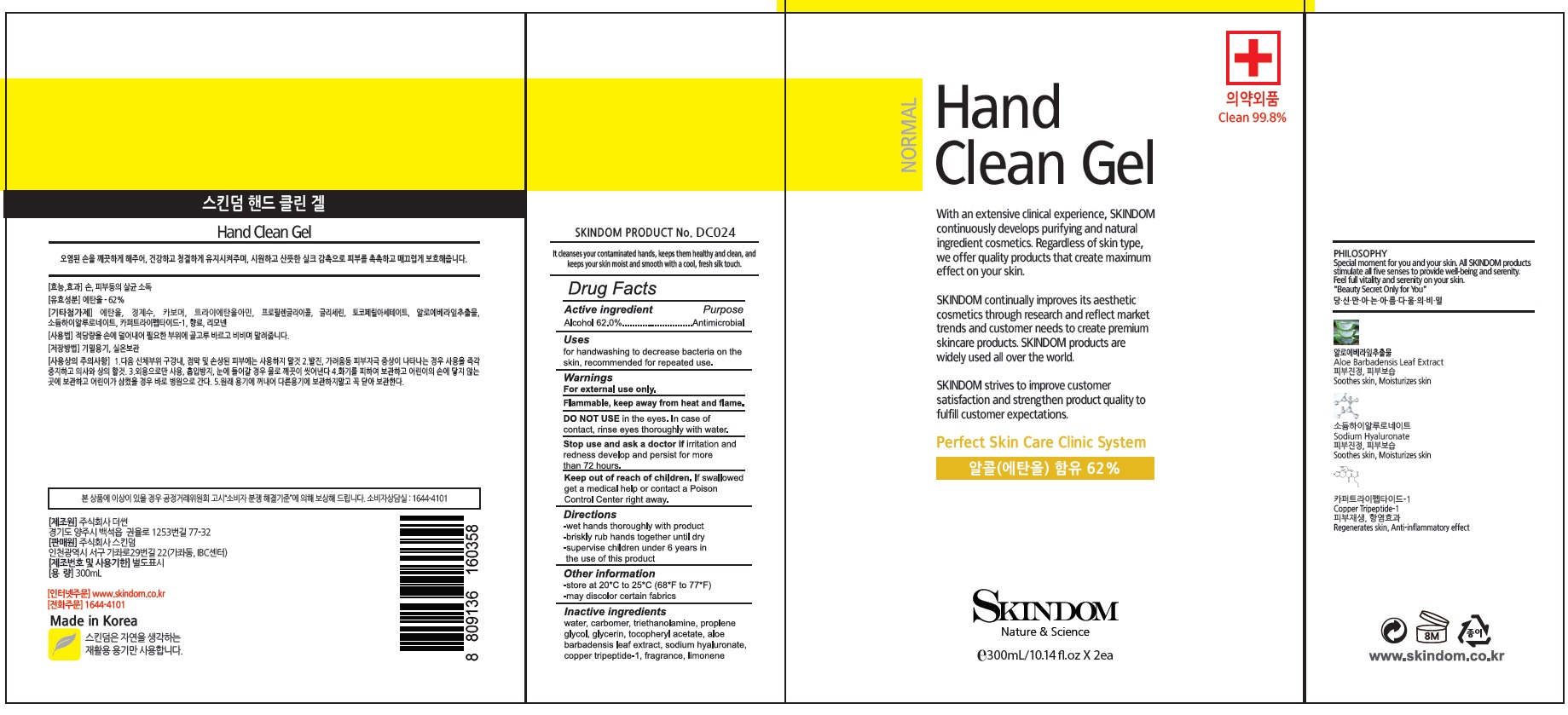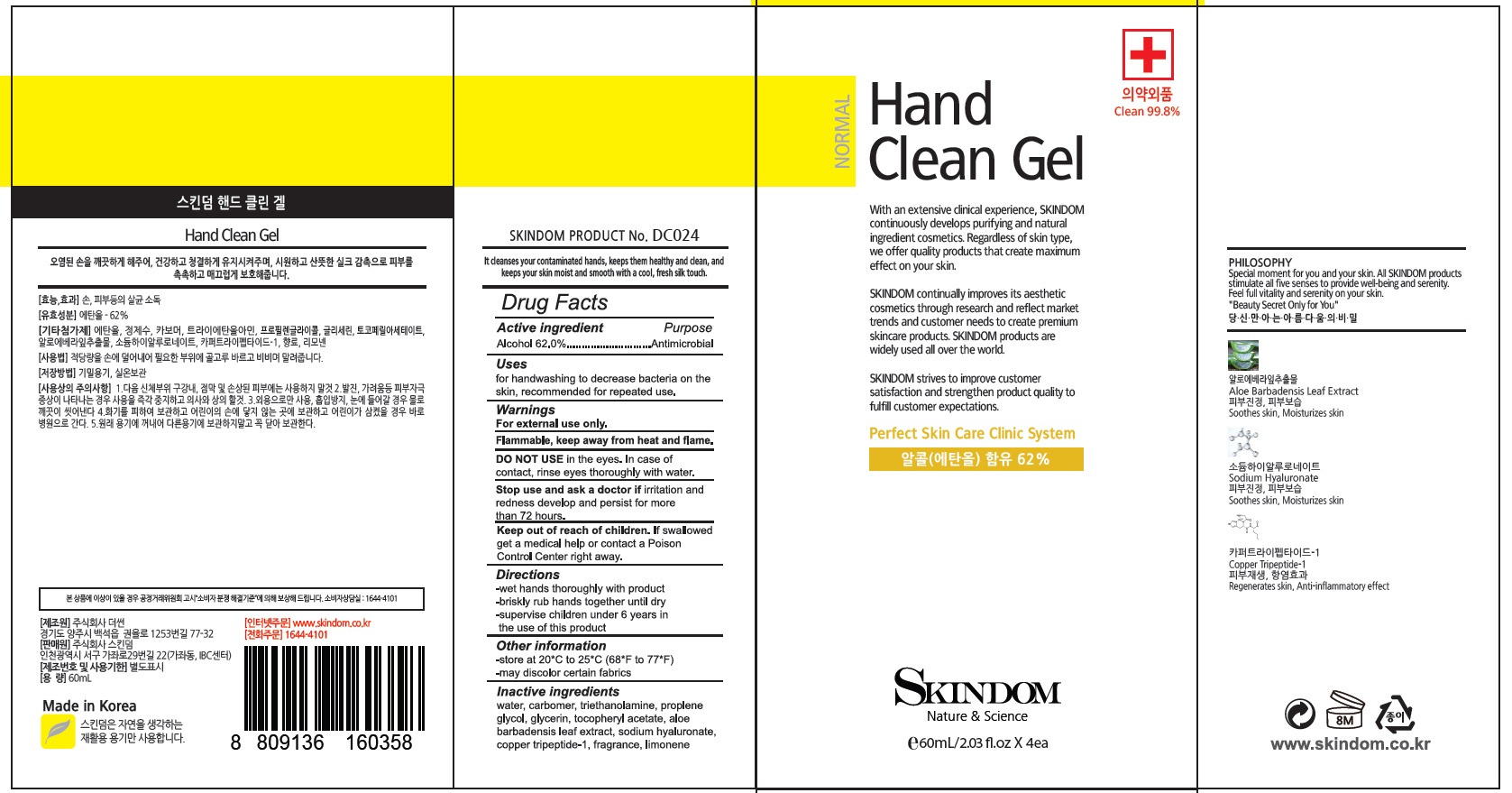 DRUG LABEL: SKINDOM Hand Clean
NDC: 74923-070 | Form: GEL
Manufacturer: THE SUN CO.LTD
Category: otc | Type: HUMAN OTC DRUG LABEL
Date: 20200501

ACTIVE INGREDIENTS: Alcohol 62 mL/100 mL
INACTIVE INGREDIENTS: Water; CARBOMER HOMOPOLYMER, UNSPECIFIED TYPE; TROLAMINE; Propylene Glycol; ALOE VERA LEAF; HYALURONATE SODIUM; PREZATIDE COPPER; LIMONENE, (+)-

ACTIVE INGREDIENT

Active ingredients: Alcohol 62.0%

INACTIVE INGREDIENT

Inactive ingredients:

Water, Carbomer, Triethanolamine, Propylene Glycol, Aloe Barbadenesis Leaf Extract, Sodium Hyaluronate, Copper Tripeptide-1, Fragrance, Limonene

PURPOSE

PURPOSE: Antimicrobial

WARNINGS

For external use only.

Flammable. Keep away from heat and flame.

DO NOT USE in the eyes. In case of contact, rinse eyes thoroughly with water

Stop use and ask a doctor if skin irritation and redness develop and persist for more than 72 hours.

KEEP OUT OF REACH OF CHILDREN

If swallowed, get medical help or contact a Poison Control Center right away.

Uses

For handwashing to decrease bacteria on the skin, recommended for repeated use

Directions

- Wet hands thoroughly with product
- Briskly rub hands together until dry
- Supervise children under 6 years in the use of this product

Other Information

- Store at 20°C to 25°C (68°F to 77°F)
- May discolor certain fabrics

QUESTIONS

www.skindom.co.kr